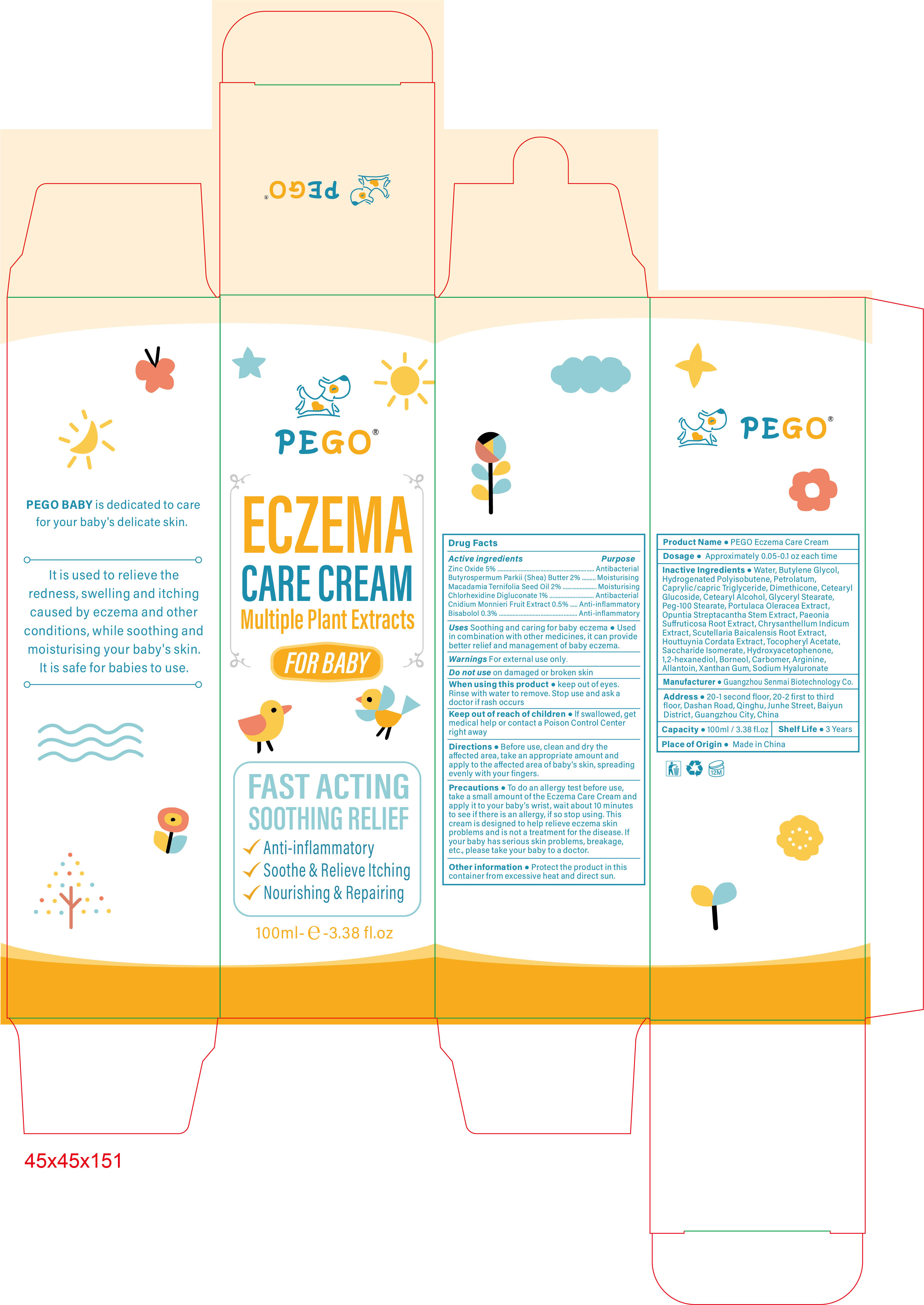 DRUG LABEL: PEGO Eczema Care Cream
NDC: 84509-041 | Form: CREAM
Manufacturer: Guangzhou Senmai Biotechnology Co.
Category: otc | Type: HUMAN OTC DRUG LABEL
Date: 20241106

ACTIVE INGREDIENTS: CNIDIUM MONNIERI FRUIT EXTRACT 500 mg/100 mL; LEVOMENOL 300 mg/100 mL; SHEA BUTTER 2000 mg/100 mL; CHLORHEXIDINE 1000 mg/100 mL; MACADAMIA OIL 2000 mg/100 mL; ZINC OXIDE 5000 mg/100 mL
INACTIVE INGREDIENTS: HYDROXYACETOPHENONE; SACCHARIDE ISOMERATE; HYALURONATE SODIUM; PAEONIA SUFFRUTICOSA ROOT; PURSLANE; BUTYLENE GLYCOL; HYDROGENATED POLYISOBUTENE (450 MW); PETROLATUM; CETEARYL GLUCOSIDE; .ALPHA.-TOCOPHEROL ACETATE; XANTHAN GUM; ALLANTOIN; WATER; SCUTELLARIA BAICALENSIS ROOT; CHRYSANTHELLUM INDICUM TOP; ARGININE; CETEARYL ALCOHOL; HOUTTUYNIA CORDATA FLOWERING TOP; PEG-100 STEARATE; GLYCERYL MONOSTEARATE; OPUNTIA STREPTACANTHA STEM; 1,2-HEXANEDIOL; BORNEOL; CARBOMER 1342; DIMETHICONE; MEDIUM-CHAIN TRIGLYCERIDES

Active Ingredients

Zinc Oxide 5%
Butyrospermum Parkii (Shea) Butter 2%
Macadamia Ternifolia Seed 0il 2%
Chlorhexidine Digluconate 1%

Cnidium Monnieri Fruit Extract 0.5%

Bisabolol 0.3%

Purpose

Antibacterial

Moisturising
Anti-inflammatory

Product Name

PEGO Eczema Care Cream

Uses Soothing and caring for baby eczema

Used in combination with other medicines, it can provide better relief and management of baby eczema.

Warnings

ror externa use only

Do not use

on damaged or broken skin

When using this product

Keep out of eyes. Rinse with water to remove. Stop use and ask a doctor if rash occurs.

Keep out of reach of children

If swallowed, get medical help or contact a Poison Control Center right away

Directions

Before use, clean and dry the affected area,take an appropriate amount and apply to the affected area of baby's skin,spreading evenly with your fingers.

Precautions

To do an allergy test before use,take a small amount of the Eczema Care Cream and apply it to your baby's wrist,wait about 10 minutes to see if there is an allergy, if so stop using.This cream is designed to help relieve eczema skin problems and is not a treatment for the disease.lf your baby has serious skin problems, breakage,etc., please take your baby to a doctor.

Other information

Protect the product in this container from excessive heat and direct sun.

Dosage

Approximately 0.05-0.1 oz each time

Inactive Ingredients

Water, Butylene Glycol,Hydrogenated Polyisobutene, Petrolatum,Caprylic/capric Triglyceride,Dimethicone, Cetearyl Glucoside,Cetearyl Alcohol, Glyceryl Stearate,Peg-100 Stearate, Portulaca Oleracea Extract,Opuntia Streptacantha Stem Extract, Paeonia Suffruticosa Root Extract,Chrysanthellum Indicum Extract,Scutellaria Baicalensis Root Extract,Houttuynia Cordata Extract,Tocopheryl
Acetate,Saccharide lsomerate,Hydroxyacetophenone,1,2-hexanediol,Borneol, Carbomer,Arginine,Allantoin,Xanthan Gum,Sodium Hyaluronate

Manufacturer

Guangzhou Senmai Biotechnology Co.

Address

20-1 second floor, 20-2 first to third floor,Dashan Road,Qinghu,Junhe Street, Baiyun district, Guangzhou City, China.

Capacity

100ml/3.38 Fl.oz

Shelf Life

3 Years

Place of Origin

Made in China